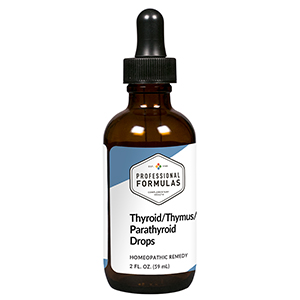 DRUG LABEL: Thyroid/Thymus/Parathyroid Drops
NDC: 63083-5029 | Form: LIQUID
Manufacturer: Professional Complementary Health Formulas
Category: homeopathic | Type: HUMAN OTC DRUG LABEL
Date: 20190815

ACTIVE INGREDIENTS: EQUISETUM ARVENSE TOP 3 [hp_X]/59 mL; CALCIUM FLUORIDE 6 [hp_X]/59 mL; ENTEROBIUS VERMICULARIS 6 [hp_X]/59 mL; HYSSOPUS OFFICINALIS WHOLE 6 [hp_X]/59 mL; THYROID, UNSPECIFIED 6 [hp_X]/59 mL
INACTIVE INGREDIENTS: ALCOHOL; WATER

HTTP

ACTIVE INGREDIENTS

Equisetum arvense 3X
Calcarea fluorica 6X
Parathyroid 6X, 12X, 30X, 60X, 100X
Thymus 6X, 12X, 30X, 60X, 100X
Thyroid 6X, 12X, 30X, 60X, 100X

QUESTIONS

Professional Formulas

PO Box 2034 Lake Oswego, OR 97035

INDICATIONS

For the temporary relief of cough, shortness of breath, mild chest pain, muscle weakness, or fatigue.*

PURPOSE

*Claims based on traditional homeopathic practice, not accepted medical evidence. Not FDA evaluated.

WARNINGS

Consult a doctor if condition worsens or if symptoms persist. Keep out of the reach of children. In case of overdose, get medical help or contact a poison control center right away. If pregnant or breastfeeding, ask a healthcare professional before use.

Keep out of the reach of children.

PREGNANCY OR BREAST FEEDING

If pregnant or breastfeeding, ask a healthcare professional before use.

DIRECTIONS

Place drops under tongue 30 minutes before/after meals. Adults and children 12 years and over: Take 10 drops up to 3 times per day. Consult a physician for use in children under 12 years of age.

OTHER INFORMATION

Tamper resistant. If seal is broken, do not use. After opening, close container tightly and store at room temperature away from heat.

INACTIVE INGREDIENTS

20% ethanol, purified water.

LABEL

Est 1985

Professional Formulas

Complementary Health

Thyroid/Thymus/Parathyroid Drops

Homeopathic Remedy

2 FL. OZ. (59 mL)